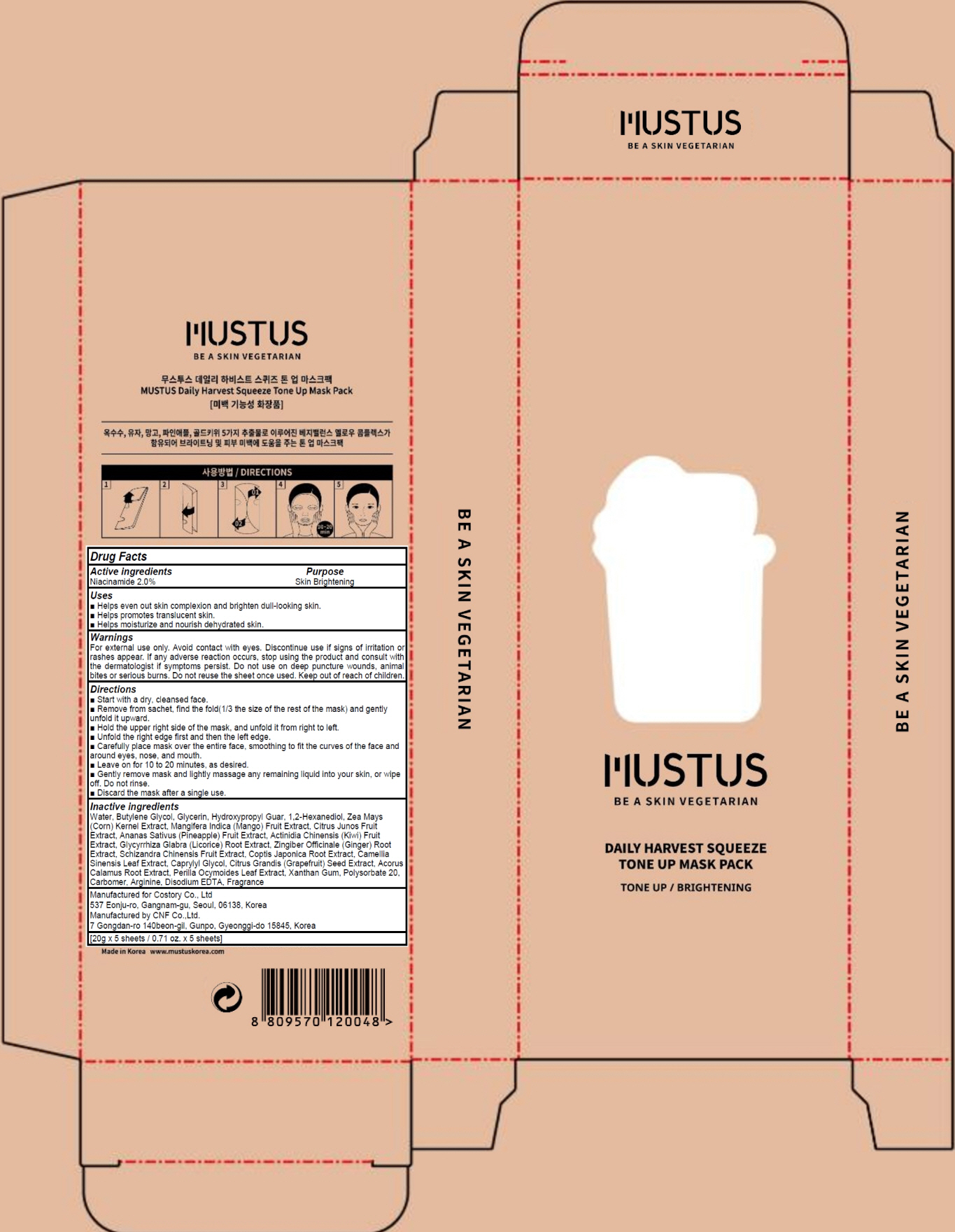 DRUG LABEL: MUSTUS DAILY HARVEST SQUEEZE TONE UP MASK PACK
NDC: 73020-010 | Form: PATCH
Manufacturer: Costory Co., Ltd
Category: otc | Type: HUMAN OTC DRUG LABEL
Date: 20190503

ACTIVE INGREDIENTS: Niacinamide 0.4 g/20 g
INACTIVE INGREDIENTS: Water; Butylene Glycol

ACTIVE INGREDIENT

Active Ingredient: Niacinamide 2.0%

INACTIVE INGREDIENT

Inactive Ingredients:

Water, Butylene Glycol, Glycerin, Hydroxypropyl Guar, 1,2-Hexanediol, Zea Mays (Corn) Kernel Extract, Mangifera Indica (Mango) Fruit Extract, Citrus Junos Fruit Extract, Ananas Sativus (Pineapple) Fruit Extract, Actinidia Chinensis (Kiwi) Fruit Extract, Glycyrrhiza Glabra (Licorice) Root Extract, Zingiber Officinale (Ginger) Root Extract, Schizandra Chinensis Fruit Extract, Coptis Japonica Root Extract, Camellia Sinensis Leaf Extract, Caprylyl Glycol, Citrus Grandis (Grapefruit) Seed Extract, Acorus Calamus Root Extract, Perilla Ocymoides Leaf Extract, Xanthan Gum, Polysorbate 20, Carbomer, Arginine, Disodium EDTA, Fragrance

PURPOSE

Purpose: Skin Brightening

WARNINGS

For external use only. Avoid contact with eyes. Discontinue use if signs of irritation or rashes appear. If any adverse reaction occurs, stop using the product and consult with the dermatologist if symptoms persist. Do not use on deep puncture wounds, animal bites or serious burns. Do not reuse the sheet once used. Keep out of reach of children.

KEEP OUT OF REACH OF CHILDREN

Uses

■ Helps even out skin complexion and brighten dull-looking skin.
■ Helps promotes translucent skin.
■ Helps moisturize and nourish dehydrated skin.

Directions

■ Start with a dry, cleansed face.
■ Remove from sachet, find the fold(1/3 the size of the rest of the mask) and gently unfold it upward.
■ Hold the upper right side of the mask, and unfold it from right to left.
■ Unfold the right edge first and then the left edge.
■ Carefully place mask over the entire face, smoothing to fit the curves of the face and around eyes, nose, and mouth.
■ Leave on for 10 to 20 minutes, as desired.
■ Gently remove mask and lightly massage any remaining liquid into your skin, or wipe off. Do not rinse.
■ Discard the mask after a single use.